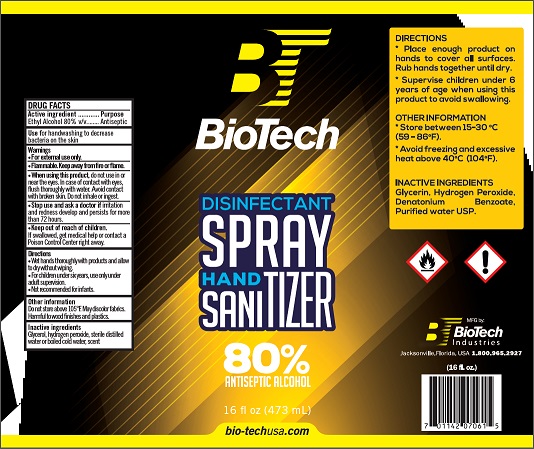 DRUG LABEL: BioTech Disinfectant Hand Sanitizer
NDC: 77791-002 | Form: LIQUID
Manufacturer: BIOTECH INDUSTRIES
Category: otc | Type: HUMAN OTC DRUG LABEL
Date: 20200516

ACTIVE INGREDIENTS: ALCOHOL 80 mL/100 mL
INACTIVE INGREDIENTS: GLYCERIN; HYDROGEN PEROXIDE; WATER

Active Ingredient

Ethyl Alcohol 80% v/v

Purpose

Antiseptic

Use

For handwashing to decrease bacteria on the skin

Warnings

For external use only.

Flammable. Keep away from heat or flame

When using this product do not use in or near the eyes. In case of contact with eyes, rinse eyes thoroughly with water. Avoid contact with broken skin. Do not inhale or ingest.

Stop use and ask a doctor if irritation and redness develop and persists for more than 72 hours.

Keep out of reach of children. If swallowed, get medical help or contact a Poison Control Center right away.

Directions

Wet hands thoroughly with products and allow to dry without wiping.

For children under six years, use only under adult supervision.

Not recommended for infants.

Inactive ingredients

Glycerol, hydrogen peroxide, sterile distilled water or boiled cold water, scent, rapid gel